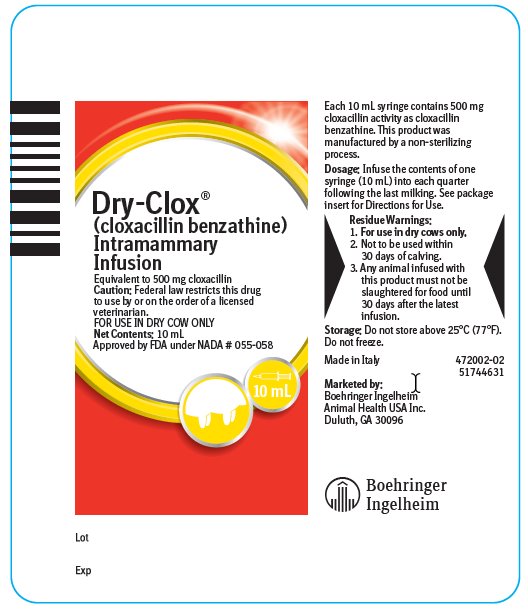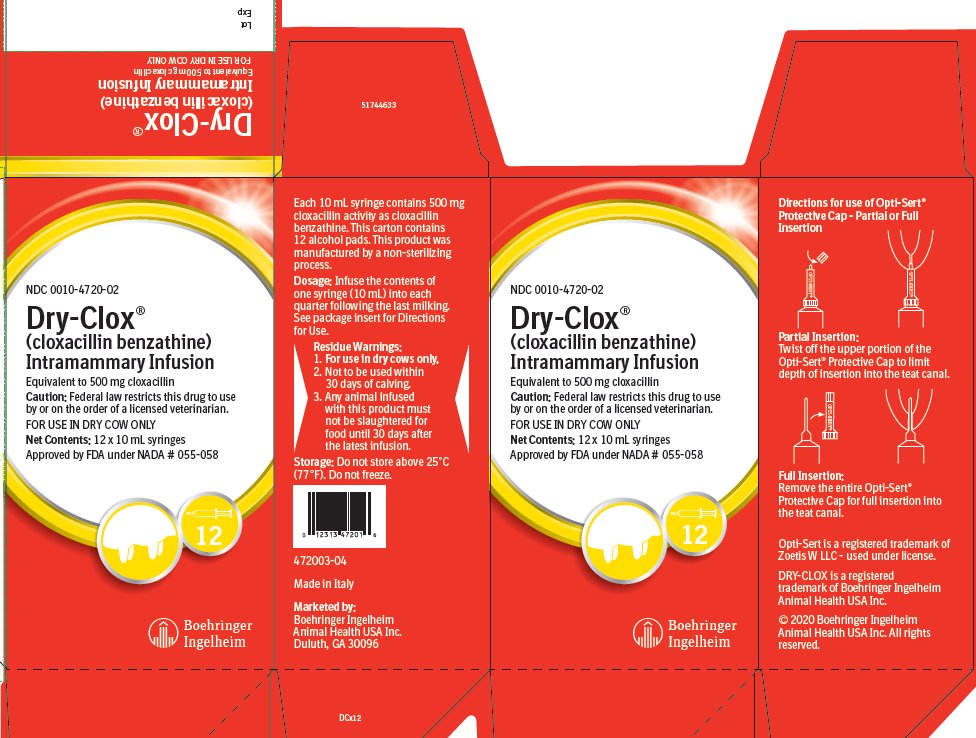 DRUG LABEL: Dry-Clox
NDC: 0010-4720 | Form: GEL
Manufacturer: Boehringer Ingelheim Animal Health USA Inc.
Category: animal | Type: PRESCRIPTION ANIMAL DRUG LABEL
Date: 20220518

ACTIVE INGREDIENTS: CLOXACILLIN BENZATHINE 500 mg/10 mL
INACTIVE INGREDIENTS: PEANUT OIL; HYDROGENATED CASTOR OIL

Dry-Clox®
(cloxacillin benzathine)
Intramammary Infusion
FOR USE IN DRY COW ONLY

Approved by FDA under NADA # 055-058

Caution:

Federal law restricts this drug to use by or on the order of a licensed veterinarian.

Description:

DRY-CLOX (cloxacillin benzathine) is a product which provides bactericidal activity against gram-positive bacteria in the dry cow. The active agent, cloxacillin benzathine, is a sparingly soluble salt of the semisynthetic penicillin, cloxacillin. Cloxacillin is a derivative of 6-aminopenicillanic acid, and therefore is chemically related to other penicillins. It has, however, the antibacterial properties described below, which distinguish it from certain other penicillins.

Each 10 mL disposable syringe contains cloxacillin benzathine equivalent to 500 mg of cloxacillin activity in a stable peanut oil gel. This product was manufactured by a non-sterilizing process.

Storage:

Do not store above 25°C (77°F). Do not freeze.

Action:

In the non-lactating mammary gland, DRY-CLOX provides bactericidal levels of the active antibiotic, cloxacillin, for a prolonged period of time. This prolonged activity is due to the low solubility of the cloxacillin benzathine and to the slow-release oil-gel base. This prolonged contact between the antibiotic and the pathogenic organism enhances the probability of a bacteriological cure.

Cloxacillin is not destroyed by the enzyme, penicillinase, and therefore, is active against penicillin-resistant strains of Staphylococcus aureus. It is also active against non-penicillinase-producing Staphylococcus aureus as well as Streptococcus agalactiae.

The class disc, Methicillin 5 mcg, should be used to estimate the in vitro susceptibility of bacteria to cloxacillin.

Indications:

For the treatment of mastitis in dairy cows during the dry period.

DRY-CLOX has been shown by extensive clinical studies to be efficacious in the treatment of mastitis in dry cows, when caused by Streptococcus agalactiae and Staphylococcus aureus including penicillin-resistant strains.

Treatment of the dry cow with DRY-CLOX is indicated in any cow known to harbor any of these organisms in the udder at drying off, or which has had repeated attacks of mastitis during the previous lactation, or is affected with mastitis at drying off, if caused by susceptible organisms.

Dosage for Dry Cows:

Infuse the contents of one syringe (10 mL) into each quarter following the last milking. See Directions for Use.

Directions for Use:

DRY-CLOX is for use in dry cows only. Administer immediately after the last milking. Use no later than 30 days prior to calving.

Completely milk out all four quarters. The udder and teats should be thoroughly washed with warm water containing a suitable dairy antiseptic and dried, preferably using individual paper towels. Carefully scrub the teat end and orifice with 70% alcohol, using a separate swab for each teat. Allow to dry.

DRY-CLOX is packaged with the Opti-Sert® Protective Cap.

For partial insertion: Twist off upper portion of the Opti-Sert® Protective Cap to expose 3–4 mm of the syringe tip.

For full insertion: Remove protective cap to expose the full length of the syringe tip.

Insert syringe tip into the teat canal and expel the entire contents of syringe into the quarter. Withdraw the syringe and gently massage the quarter to distribute the medication.

Do not infuse contents of the mastitis syringe into the teat canal if the Opti-Sert® Protective Cap is broken or damaged.

Precautions:

Because it is a derivative of 6-aminopenicillanic acid, DRY-CLOX has the potential for producing allergic reactions. Such reactions are rare; however, should they occur, the subject should be treated with antihistamines or pressor amines, such as epinephrine.

Residue Warnings:

1. For use in dry cows only.

2. Not to be used within 30 days of calving.

3. Any animal infused with this product must not be slaughtered for food until 30 days after the latest infusion.

How Supplied:

DRY-CLOX (cloxacillin benzathine) is supplied as 10 mL syringes containing 500 mg of cloxacillin activity per syringe. One display carton contains 12 syringes. One pail contains 144 syringes.

NDC 0010-4720-02 - 12 syringes
NDC 0010-4720-03 - 144 syringes

Opti-Sert is a registered trademark of Zoetis W LLC - used under license.

DRY-CLOX is a registered trademark of Boehringer Ingelheim Animal Health USA Inc.

© 2020 Boehringer Ingelheim Animal Health USA Inc. All rights reserved.

Made in Italy

Marketed by:
Boehringer Ingelheim Animal Health USA Inc.
Duluth, GA 30096

51744632

472001-04

Principal Display Panel – Syringe Label

Dry-Clox®

(cloxacillin benzathine)

Intramammary Infusion

Equivalent to 500 mg cloxacillin

Caution: Federal law restricts this drug to use by or on the order of a licensed veterinarian.

FOR USE IN DRY COW ONLY

Net Contents: 10 mL

Approved by FDA under NADA # 055-058

Principal Display Panel – 12 x 10 mL display carton

NDC 0010-4720-02

Dry-Clox®

(cloxacillin benzathine)

Intramammary Infusion

Equivalent to 500 mg cloxacillin

Caution: Federal law restricts this drug to use by or on the order of a licensed veterinarian.

FOR USE IN DRY COW ONLY

Net Contents: 12 x 10 mL syringes

Approved by FDA under NADA # 055-058